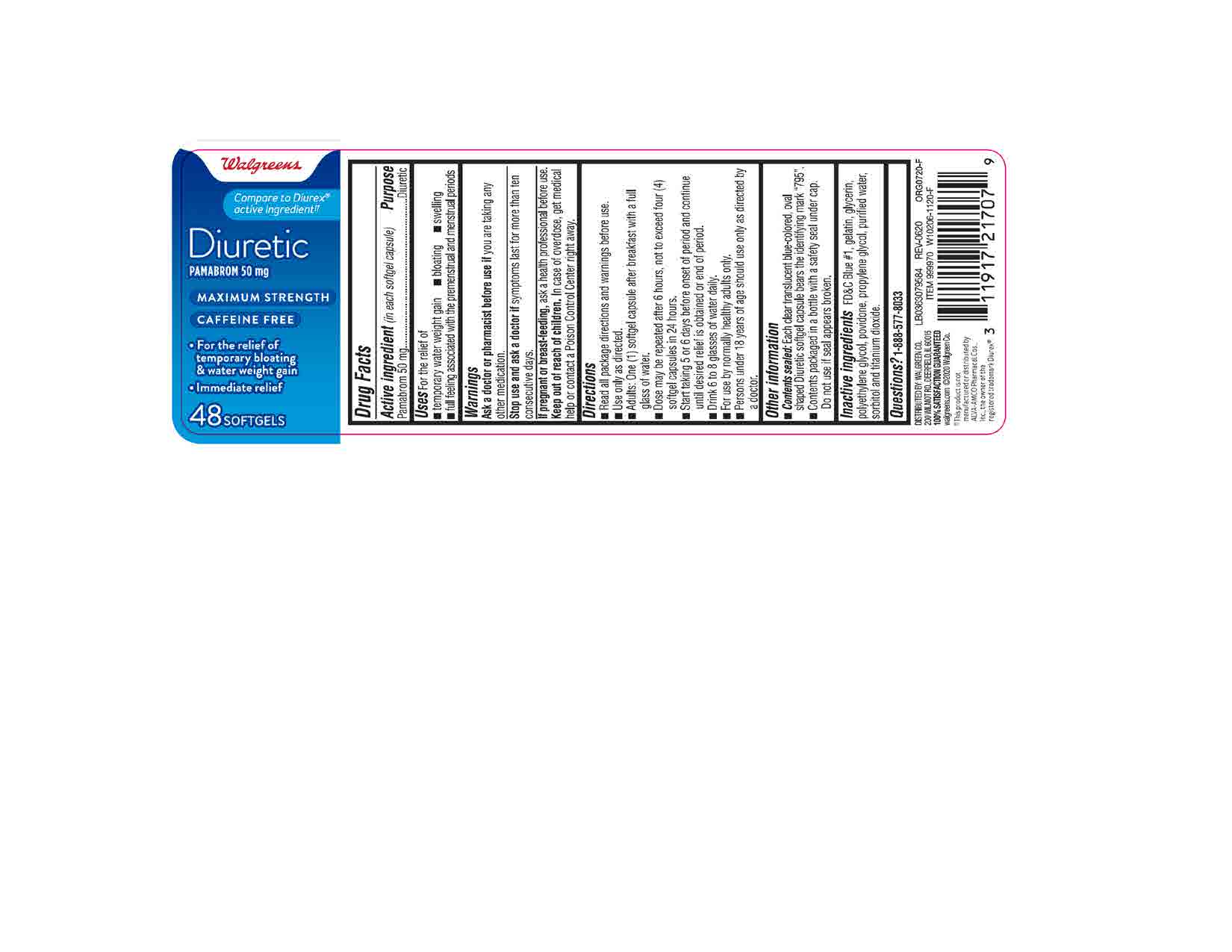 DRUG LABEL: Pamabrom
NDC: 0363-0795 | Form: CAPSULE, LIQUID FILLED
Manufacturer: WALGREENS CO.
Category: otc | Type: HUMAN OTC DRUG LABEL
Date: 20240115

ACTIVE INGREDIENTS: PAMABROM 50 mg/1 1
INACTIVE INGREDIENTS: WATER; FD&C BLUE NO. 1; POLYETHYLENE GLYCOL 400; SORBITOL; PROPYLENE GLYCOL; GLYCERIN; GELATIN, UNSPECIFIED; POVIDONE K30; TITANIUM DIOXIDE

Sleep-Aid
Diphenhydramine HCl 25mg (Purple Softgel)

ACTIVE INGREDIENT

Pamabrom 50mg

PURPOSE

Diuretic

INACTIVE INGREDIENT

FD&C Blue#1, gelatin, glycerin, polyethylene glycol, povidone, propylene glycol, purified water, sorbitol and titanium dioxide

DOSAGE AND ADMINISTRATION

Read all package direction and warnings before use.

Use only as directed.

Adults: One(1) softgel capsule after breakfast with a full glass of water.

Dose may be repeated after 6 hours, not to exceed four (4) softgel capsules in 24 hours.

Start taking 5 or 6 days before onset of period and continue until desired relief is obtained or end of period.

Drink 6 to 8 glasses of water daily.

For use by normally healthy adults only

Persons under 18 years of age should use only as directed by a doctor.

INDICATIONS AND USAGE

For the relief of

temporary water wieght gain

bloating

swelling

full feling associated with the premenstrual and menstrual periods

Ask a doctor or pharmacist before use if you are taking any other medication.

Stop use and ask a doctor if symptoms last for more than ten consecutive days.

If pregnant or breast-feeding, ask a health professional before use.

Keep out of reach of children. In case of overdose, get medical help or contact a poison control center right away.

Keep out of reach of children.

OVERDOSAGE

In case of overdose, get medical help or contact a Poison Control Center right away.

OTHER SAFETY INFORMATION

Contents sealed: Each clear translucent blue-colored, oval shaped Diuretic softgel capsule bears the identifying mark "795".

Contents packaged ina bottle with a safety seal under cap. Do not use if seal appears broken.